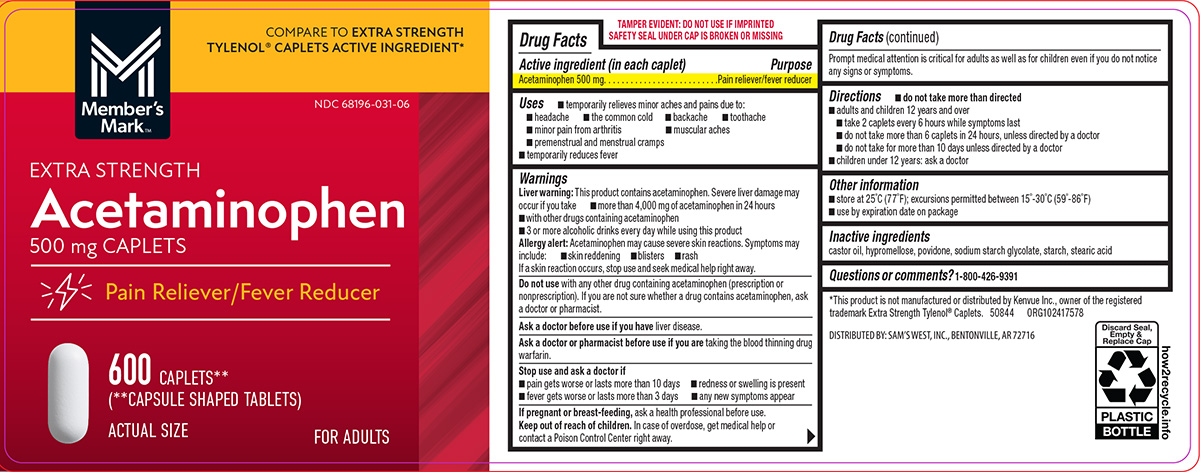 DRUG LABEL: Acetaminophen
NDC: 68196-031 | Form: TABLET, FILM COATED
Manufacturer: Sam's West Inc
Category: otc | Type: HUMAN OTC DRUG LABEL
Date: 20251023

ACTIVE INGREDIENTS: ACETAMINOPHEN 500 mg/1 1
INACTIVE INGREDIENTS: CASTOR OIL; HYPROMELLOSE, UNSPECIFIED; POVIDONE, UNSPECIFIED; SODIUM STARCH GLYCOLATE TYPE A POTATO; STARCH, CORN; STEARIC ACID

Pain Reliever

Active ingredient (in each caplet)

Acetaminophen 500 mg

Purpose

Pain reliever/fever reducer

Uses

- temporarily relieves minor aches and pains due to:
  - headache
  - muscular aches
  - the common cold
  - backache
  - toothache
  - minor pain from arthritis
  - premenstrual and menstrual cramps
- temporarily reduces fever

Warnings

Liver warning: This product contains acetaminophen. Severe liver damage may occur if you take

- more than 4,000 mg of acetaminophen in 24 hours
- with other drugs containing acetaminophen
- 3 or more alcoholic drinks every day while using this product

Allergy alert: Acetaminophen may cause severe skin reactions. Symptoms may include:

- rash
- skin reddening
- blisters

If a skin reaction occurs, stop use and seek medical help right away.

Do not use

with any other drug containing acetaminophen (prescription or nonprescription). If you are not sure whether a drug contains acetaminophen, ask a doctor or pharmacist.

Ask a doctor before use if you have

liver disease.

Ask a doctor or pharmacist before use if you are

taking the blood thinning drug warfarin.

Stop use and ask a doctor if

- redness or swelling is present
- pain gets worse or lasts more than 10 days
- fever gets worse or lasts more than 3 days
- any new symptoms appear

If pregnant or breast-feeding,

ask a health professional before use.

Keep out of reach of children.

In case of overdose, get medical help or contact a Poison Control Center right away. Prompt medical attention is critical for adults as well as for children even if you do not notice any signs or symptoms.

Directions

- do not take more than directed
- adults and children 12 years and over
  - take 2 caplets every 6 hours while symptoms last
  - do not take more than 6 caplets in 24 hours, unless directed by a doctor
  - do not take for more than 10 days unless directed by a doctor
- children under 12 years: ask a doctor

Other information

- store at 25°C (77°F); excursions permitted between 15°-30°C (59°-86°F)
- use by expiration date on package

Inactive ingredients

castor oil, hypromellose, povidone, sodium starch glycolate, starch, stearic acid

Questions or comments?

1-800-426-9391

Principal Display Panel

COMPARE TO EXTRA STRENGTH
TYLENOL® CAPLETS ACTIVE INGREDIENT*

M
Member's
Mark™

NDC 68196-031-06

EXTRA STRENGTH

Acetaminophen
500 mg CAPLETS

Pain Reliever/Fever Reducer

600 CAPLETS**
(**CAPSULE SHAPED TABLETS)

ACTUAL SIZE
FOR ADULTS

TAMPER EVIDENT: DO NOT USE IF IMPRINTED
SAFETY SEAL UNDER CAP IS BROKEN OR MISSING

*This product is not manufactured or distributed by Kenvue Inc., owner of the registered
trademark Extra Strength Tylenol® Caplets. 50844 ORG102417578

DISTRIBUTED BY: SAM'S WEST, INC., BENTONVILLE, AR 72716

members mark 44-175